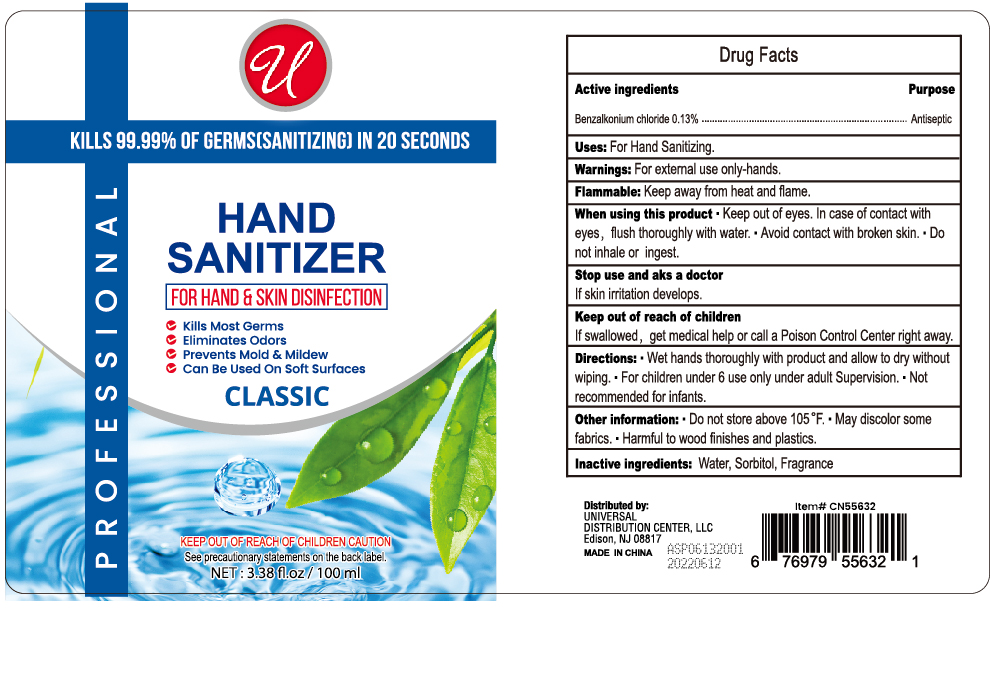 DRUG LABEL: U HAND SANITIZER CLASSIC
NDC: 72119-004 | Form: SOLUTION
Manufacturer: BLUE SEA AEROSOL & DAILY CARE CO., LTD
Category: otc | Type: HUMAN OTC DRUG LABEL
Date: 20241206

ACTIVE INGREDIENTS: BENZALKONIUM CHLORIDE 0.13 g/100 mL
INACTIVE INGREDIENTS: SORBITOL; WATER

72119-004

Active Ingredient(s)

Benzalkonium Chloride 0.13%

Purpose

Antiseptic

Use

For Hand Sanitizing

Warnings

For external use only - Hands

When using this product keep out of eyes. In case of contact with eyes, flush thoroughly with water.

Avoid contact with broken skin

Do not inhale or ingest

Stop use and ask a doctor if skin irritation develops

Keep out of reach of children. If swallowed, get medical help or call a Poison Control Center right away.

Directions

- Wet hands thoroughly with product and rub until dry without wiping
- For children under 6, use only under adult supervision
- Not recommended for infants

Other information

Do not store above 105F

May discolor some fabrics

Harmful to wood finishes and plastics

Inactive ingredients

Water, Sorbitol, Fragrance